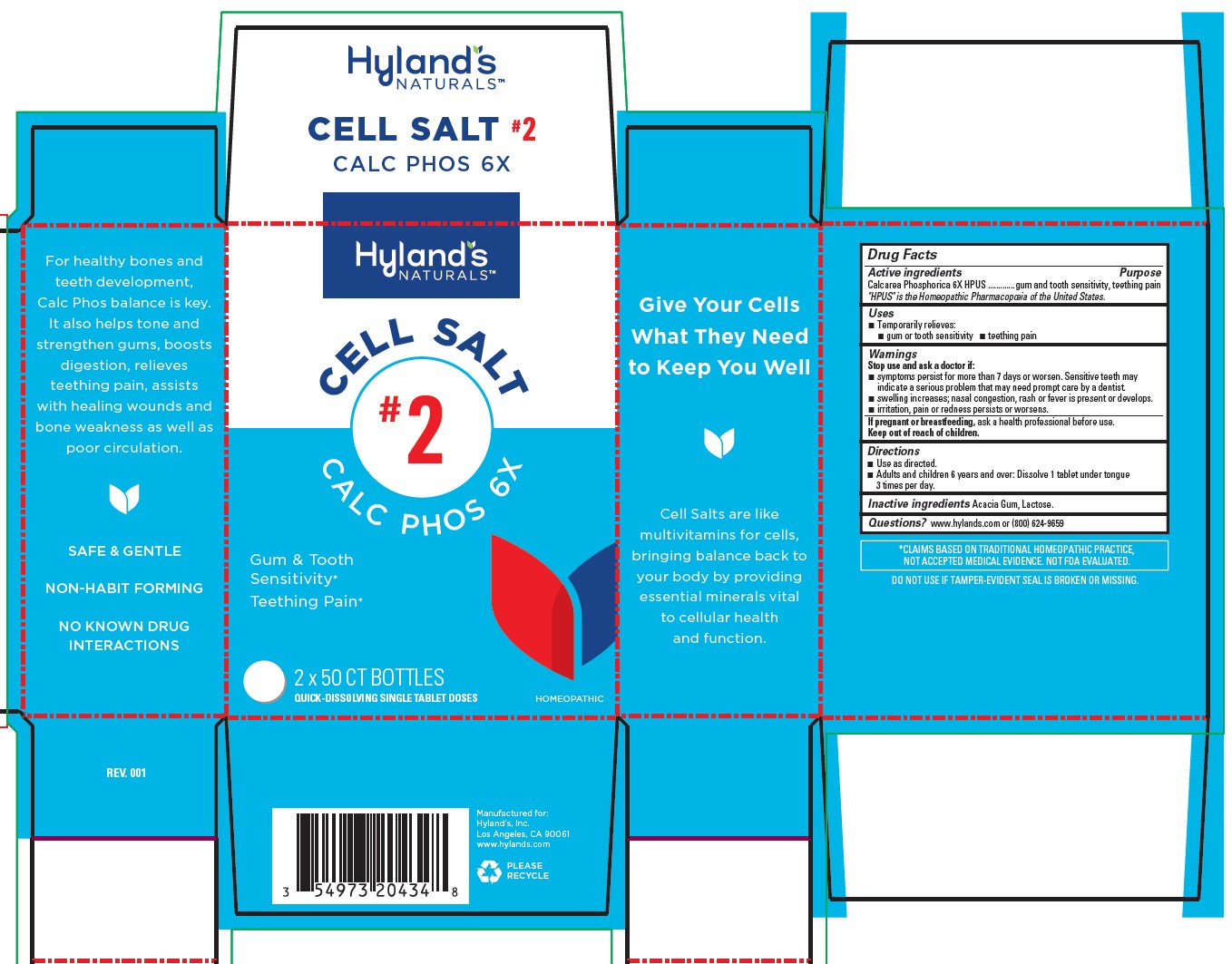 DRUG LABEL: Calc Phos
NDC: 54973-4073 | Form: TABLET
Manufacturer: Hyland's Inc.
Category: homeopathic | Type: HUMAN OTC DRUG LABEL
Date: 20221207

ACTIVE INGREDIENTS: TRIBASIC CALCIUM PHOSPHATE 6 [hp_X]/1 1
INACTIVE INGREDIENTS: LACTOSE MONOHYDRATE; ACACIA

Hyland's Naturals Cell Salt #2 Calc Phos 6X

PURPOSE

Gum & Tooth Sensitivity, Teething Pain

Drug Facts

Active ingredients

Active ingredients | Purpose
Calcarea Phosphorica 6X HPUS | gum and tooth sensitivity, teething pain

"HPUS" is the Homeopathic Pharmacopoeia of the United States.

Uses

■ Temporarily relieves:
■ gum or tooth sensitivity ■ teething pain

Warnings

Stop use and ask a doctor if

■ symptoms persist for more than 7 days or worsen. Sensitive teeth may indicate a serious problem that may need prompt care by a dentist. ■ swelling increases; nasal congestion, rash or fever is present or develops. ■ irritation, pain or redness persists or worsens.

If pregnant or breastfeeding

ask a health professional before use.

Directions

■ Use as directed.
■ Adults and children 6 years and over: Dissolve 1 tablet under tongue 3 times per day.

Inactive ingredients

Acacia Gum, Lactose.

Questions?

www.hylands.com or (800) 624-9659

PACKAGE LABEL - 2 x 50 CT TABLET BOTTLES CARTON

Hyland's

NATURALS™

CELL SALT

#2

CALC PHOS 6X

Gum & Tooth
Sensitivity*
Teething Pain*

2 x 50 CT BOTTLES

QUICK-DISSOLVING SINGLE TABLET DOSES

HOMEOPATHIC